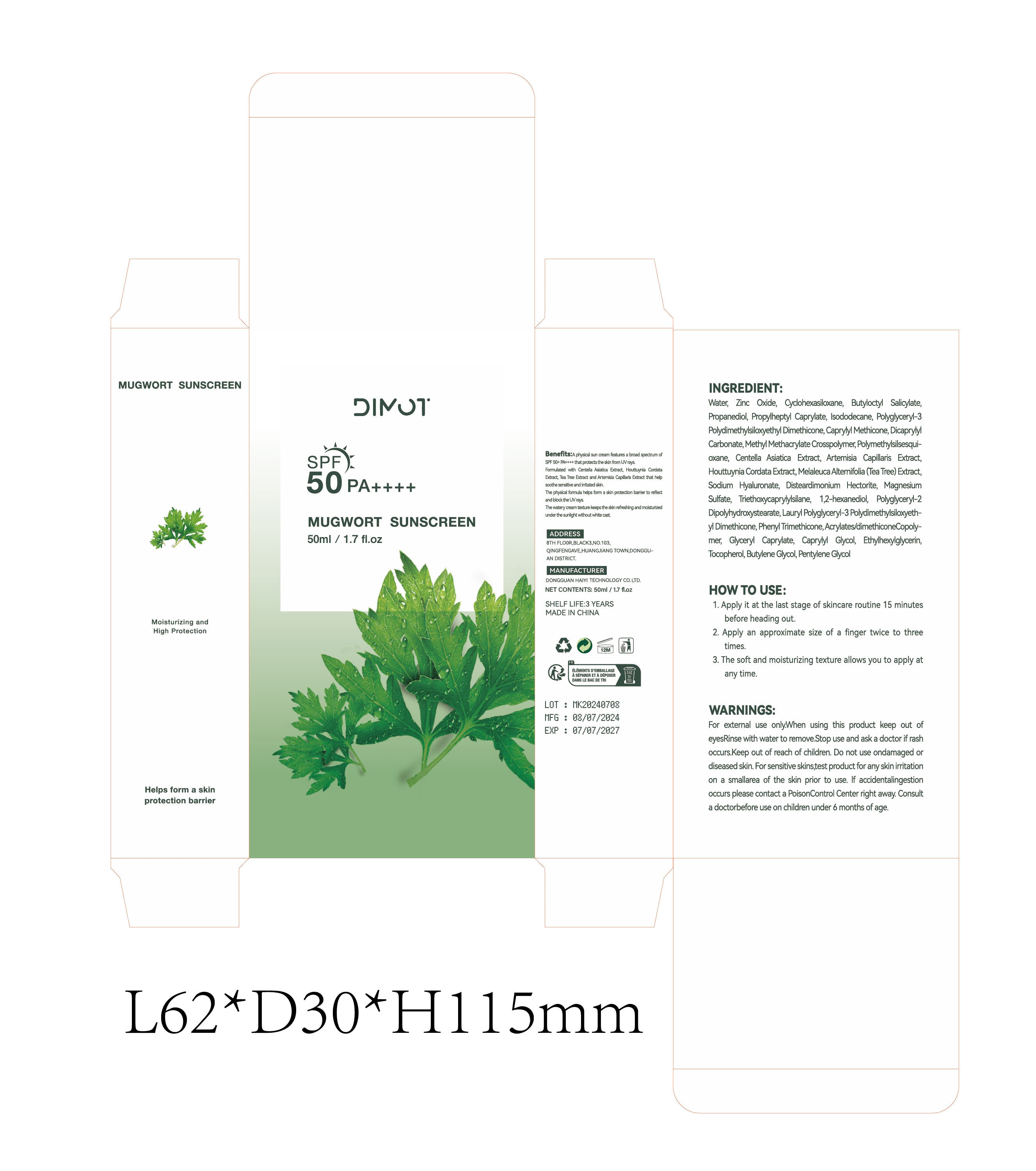 DRUG LABEL: MUGWORT SUNSCREEN
NDC: 84732-017 | Form: CREAM
Manufacturer: Dongguan Haiyi Technology Co.,Ltd.
Category: otc | Type: HUMAN OTC DRUG LABEL
Date: 20240926

ACTIVE INGREDIENTS: WATER 1 mg/50 mL
INACTIVE INGREDIENTS: ZINC OXIDE; CYCLOMETHICONE 6; ISODODECANE; POLYGLYCERIN-3; BUTYLOCTYL SALICYLATE; PROPYLHEPTYL CAPRYLATE; PROPANEDIOL

Active ingredient

Water

Inactive ingredient

Zinc Oxide,Cycohexasiloxane, Butylocty Salicylate,Propanediol, Propyheptyl Caprylate, lsododecane, Polyglycery1-3Polydimethylsiloxyethyl Dimethicone, Caprylyl Methicone, DicaprylyCarbonate, Methyl Methacrylate Crosspolymer, Polymethylsilsesqui-oxane, Centella Asiatica Extract, Artemisia Capilaris Extract,Houttuyia Cordata Extract, Melaleuca Alterifolia (Tea Tree) Extract,Sodium Hyaluronate, Disteardimonium Hectorite, MagnesiumSulfate, Triethoxycaprylylsilane,1,2-hexanediol, Polyglycery1-2Dipolyhydroxystearate, Laury! Polyglycery!-3 Polydimethylsiloxyeth-y Dimethicone, Phenyl Trimethicone, Acrylates/dimethiconeCopolymer, Glyceryl Caprylate, Caprylyl Glycol, Ethylhexylglycerin,Tocopherol, Butylene Glycol, Pentylene Glycol

Purpose section

A physical sun cream features a broad spectrum ofSPF 50+ PA++++ that protects the skin fom UV rays.Fomulated with Centella Asiatica Extract, Houttuynia CordataExtract, Tea Tree Extract and Artemisia Capillaris Exract that helpsoothe sensitive and irritated skin.The physical formula helps for a skin protection barier to reflectand block the UV rays.
The watery cream texture keeps the skin refreshing and molsturizedunder the sunlight without white cast.

Warning

For external use onlyWhen using this product keep out ofeyesRinse with water to remove.Stop use and ask a doctor if rashoccurs.Keep out of reach of children. Do not use ondamaged ordiseased skin. For sensitive skins,test product for any skin irritationon a smallarea of the skin prior to use. lf accidentalingestionoccurs please contact a PoisonControl Center right away. Consulta doctorbefore use on children under 6 months of age.

stop use

This product may cause allergic reactions in asmall number of people.
lf youexperience any discomfort,please stop using it immediately.

not use

Not suitable for use by children, pregnantor breastfeeding people.

OUT OF CHILDREN

KEEP THE PRODUCT OUT OF REACH OF CHILDREN to

HOW TO USE

1. Apply it at the last stage of skincare routine 15 minutesbefore heading out.
2. Apply an approximate size of a finger twice to threetimes.
3. The soft and moisturizing texture allows you to apply atany time.

Dosage

take an appropriateamount,Use 2-3 times a week